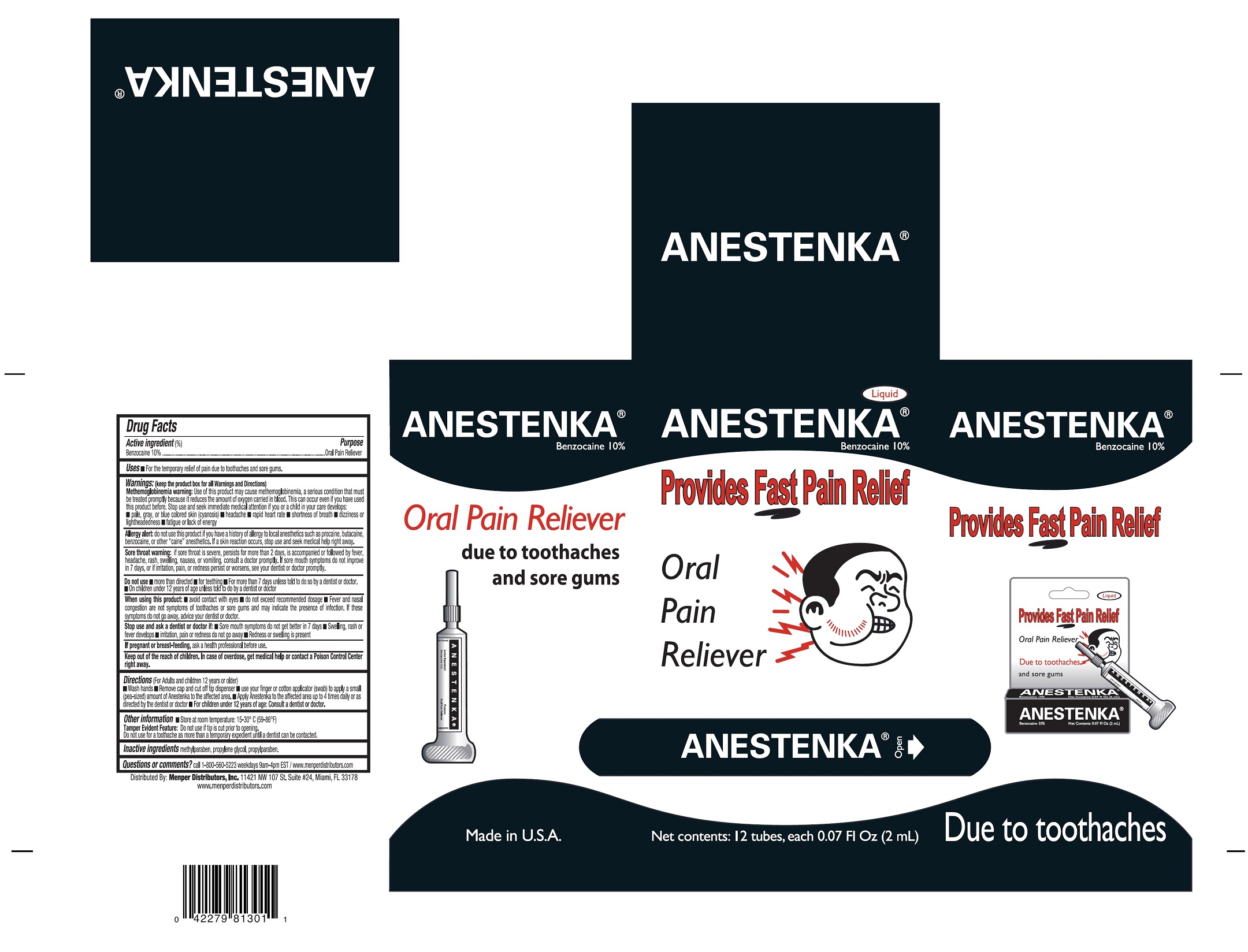 DRUG LABEL: Anestenka
NDC: 53145-301 | Form: LIQUID
Manufacturer: Menper Distributors, Inc
Category: otc | Type: HUMAN OTC DRUG LABEL
Date: 20250722

ACTIVE INGREDIENTS: BENZOCAINE 0.2 mg/2 mL
INACTIVE INGREDIENTS: METHYLPARABEN; PROPYLENE GLYCOL; PROPYLPARABEN

Anestenka

active Ingrediets(%)

Benzocaine 10%

Purpose

Oral Pain Reliever

Uses

For temporary relief of pain due to toothaches and sure gums.

methemoglobinemia warning:

Use of this product may cause methemoglobinemia, a seious condition that must be treated promtly because it reduces the amount of oxygen carried in blood. This can occurred even if you have used this product before. Stop used and seek immediate medical attention if you or a child in your care develops:

- pale, gray, or blue colored skin (cyanosis)
- headache
- rapid hear rate
- shortness of breath
- dizziness or lightheadedness
- fatigue or lack of energy

Allergy alert:

do not use this product if you have a history of allergy to local anesthethics such as procaine, butacaine, benzocaine, or other "caine" anesthetic. If skin reacction ocurrs, stop use and seek medical help right away.

Sore throat warning:

if sore throat is severe, persists for more that two days, is accompanied or followed by fever, headache, rash, swelling, nausea, or vomiting, consult a doctor promptly. If sore mouth symptoms do not improve in 7 days, or if irritation, pain, or redness persist or worsens, see your dentist dentist or doctor promptly.

Do not use:

- more than directed
- for teething
- for more than 7 days unless told to do so by a dentist or doctor
- on child under 12 years of age unless told to do so by a dentist or doctor

When using this product:

- Avoid contact with eyes
- do not exceed recomended dosage
- fever and nasal congestion are not symptoms of toothache or sore gums and may indicate the presence of infection. If these symptoms do not go away, advise your dentist or doctor.

Stop use and ask dentist or doctor if :

- Sore mouth symptoms do not get better in 7 days
- swelling, rash or fever develops
- irritation, pain, or redness do not go away
- Redness or swelling is presented

If pregnant or breast-feeeding

ask a health professional before use.

Keep out of reach of children,

In case of overdose, get medical help or contact a Poison Control Center right away.

Directions:

(For adults and children 12 years or older)

- wash hands
- Remove cap and cut off tip dispenser
- use your finger or cotton applicator (swab) to apply a small (pea-size) amount of Anestenka to the affected area
- Apply Anestenka to the affected area up to 4 times daily or as directed by the demtist or doctor
- For children 12 years of age: Consult a dentist or doctor

Other information:

Store at room temperature: 15-30° C (59-86° F)

Tamper Evident Feature:

Do not use if tip is cut prior to opening.

Do not use for toothache as more than a temporary expedient until a dentidst can be contacted.

Inactive Ingredients:

methylparaben, propylene glycol, propyparaben

Questions or comments?

call 1-800-560-5223 weekdays 9am-4pm EST/www.menperdistributors.com